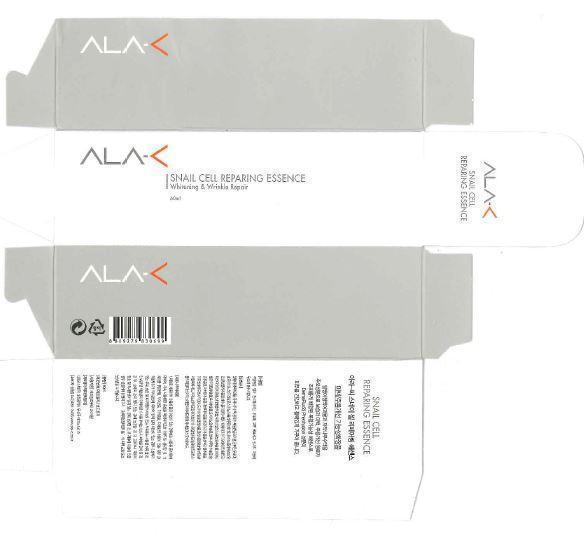 DRUG LABEL: ALA-C Snail Cell Reparing Essence 
NDC: 70091-2001 | Form: LIQUID
Manufacturer: DAOOMCOSTECH.co.Ltd.
Category: otc | Type: HUMAN OTC DRUG LABEL
Date: 20150903

ACTIVE INGREDIENTS: NIACINAMIDE 2 g/100 mL
INACTIVE INGREDIENTS: WATER; SALICYLIC ACID

Drug Facts

ACTIVE INGREDIENT

niacinamide

INACTIVE INGREDIENT

water, salicylic acid, butylene glycol, etc.

PURPOSE

skin protectant

keep out of reach of the children

INDICATIONS AND USAGE

apply proper amount to the skin

WARNINGS

do not sallow

DOSAGE AND ADMINISTRATION

for external use only